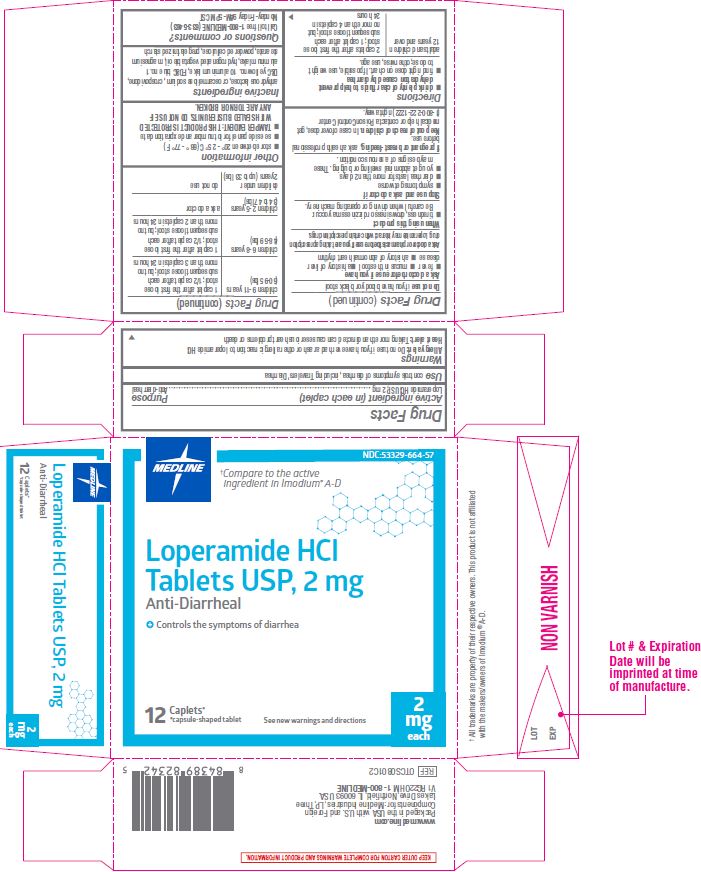 DRUG LABEL: Loperamide Hydrochloride
NDC: 53329-664 | Form: TABLET
Manufacturer: Medline Industries, LP
Category: otc | Type: HUMAN OTC DRUG LABEL
Date: 20241229

ACTIVE INGREDIENTS: LOPERAMIDE HYDROCHLORIDE 2 mg/1 1
INACTIVE INGREDIENTS: ANHYDROUS LACTOSE; CROSCARMELLOSE SODIUM; CROSPOVIDONE; D&C YELLOW NO. 10; FD&C BLUE NO. 1; TRISTEARIN; MAGNESIUM STEARATE; POWDERED CELLULOSE; STARCH, PREGELATINIZED CORN

664 Loperamide Hydrochloride

Active ingredient (in each caplet)

Loperamide HCl USP, 2 mg

Purpose

Anti-diarrheal

Use

controls symptoms of diarrhea, including Travelers' Diarrhea

Warnings

Allergy alert:Do not use if you have ever had a rash or other allergic reaction to loperamide HCI
Heart alert:Taking more than directed can cause serious heart problems or death

Do not use if

you have bloody or black stool

Ask a doctor before use if you have

- fever
- mucus in the stool
- a history of liver disease
- a history of abnormal heart rhythm

Ask a doctor or pharmacist before use if

you are taking a prescription drug. Loperamide may interact with certain prescription drugs.

When using this product

- tiredness, drowsiness or dizziness may occur. Be careful when driving or operating machinery.

Stop use and ask a doctor if

- symptoms get worse
- diarrhea lasts for more than 2 days
- you get abdominal swelling or bulging.

These may be signs of a serious condition.

If pregnant or breast-feeding,

ask a health professional before use.

Keep out of reach of children.

In case of overdose, get medical help or contact a Poison Control Center (1-800-222-1222) right away.

Directions

- drink plenty of clear fluids to help prevent dehydration caused by diarrhea
- find right dose on chart. If possible, use weight to dose; otherwise, use age.

adults and children 12 years and over | 2 caplets after the first loose stool; 1 caplet after each subsequent loose stool; but no more than 4 caplets in 24 hours
children 9-11 years; (60-95 lbs) | 1 caplet after the first loose stool; 1/2 caplet after each subsequent loose stool; but no more than 3 caplets in 24 hours
children 6-8 years; (48-59 lbs) | 1 caplet after the first loose stool; 1/2 caplet after each subsequent loose stool; but no more than 2 caplets in 24 hours
children 2-5 years; (34-47 lbs) | ask a doctor
children under 2 years; (up to 33 lbs) | do not use

Other information

- store between 20° - 25° C (68° - 77° F)
- see side panel for lot number and expiration date
- TAMPER EVIDENT: THIS PRODUCT IS PROTECTED WITH SEALED BLISTER UNITS. DO NOT USE IF ANY ARE TORN OR BROKEN.

Inactive ingredients

anhydrous lactose, croscarmellose sodium, crospovidone, D&C yellow no. 10 aluminum lake, FD&C blue no. 1 aluminum lake, hydrogenated vegetable oil, magnesium stearate, powdered cellulose, pregelatinized starch

Questions or comments?

Call toll free 1-800-MEDLINE (633-5463)
Monday-Friday 9AM-5PM CST

Manufacturing Information

Packaged for:
Medline Industries, LP
Three Lakes Drive, Northfield, IL 60093 USA
Packaged in USA with domestic and foreign materials
www.medline.com
1-800-MEDLINE (633-5463)
REF: OTCS0801C2
V1 RG22OHM